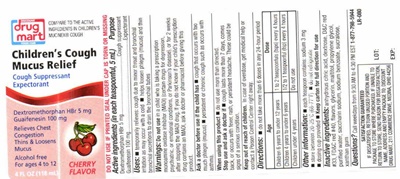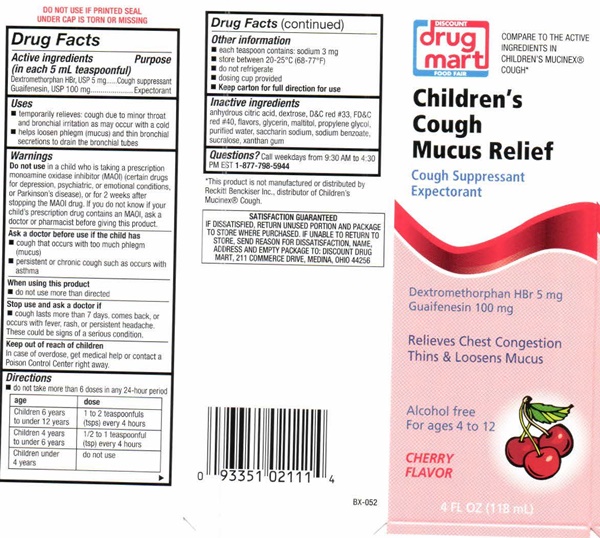 DRUG LABEL: Childrens Cough Mucus Relief
NDC: 53943-512 | Form: LIQUID
Manufacturer: Discount Drug Mart
Category: otc | Type: HUMAN OTC DRUG LABEL
Date: 20231229

ACTIVE INGREDIENTS: DEXTROMETHORPHAN HYDROBROMIDE 5 mg/5 mL; GUAIFENESIN 100 mg/5 mL
INACTIVE INGREDIENTS: ANHYDROUS CITRIC ACID; DEXTROSE; D&C RED NO. 33; FD&C RED NO. 40; GLYCERIN; MALTITOL; PROPYLENE GLYCOL; WATER; SACCHARIN SODIUM; SODIUM BENZOATE; SUCRALOSE; XANTHAN GUM

Children's Cough Mucus Relief 512

Drug Facts Active ingredients (in each 5 mL teaspoonful)

Dextromethorphan HBr, USP 5 mg
Guaifenesin, USP 100 mg

Purpose

Cough suppressant
Expectorant

Uses

- temporarily relieves: cough due to minor throat and bronchial irritation as may occur with a cold
- helps loosen phlegm (mucus) and thin bronchial secretions to drain the bronchial tubes

Warnings

Do not use in a child who is taking a prescription monoamine oxidase inhibitor (MAOI) (certain drugs for depression, psychiatric, or emotional conditions , or Parkinson's disease), or for 2 weeks after stopping the MAOI drug. if you do not know if your child's prescription drug contains an MAOI, ask a doctor or pharmacist before giving this product.

Ask a doctor before use if the child has

- cough that occurs with too much phlegm (mucus)
- persistant or chronic cough such as occurs with asthma

When using this product

- do not use more than directed

Stop use and ask a doctor if

- cough lasts more than 7 days, comes back, or occurs with fever, rash, or persistant headache.

These could be signs of a serious condition.

Keep out of reach of children.

In case of overdose, get medical help or contact a Poison Control Center right away

Directions

- do not take more than 6 doses in any 24-hour period

age dose

Children 6 years to 12 years 1 to 2 teaspoonfuls (tsps) every 4 hours
Children 4 years to under 6 years 1/2 to 1 teaspoonful (tsps) every 4 hours
Children under 4 years do not use

Other information

- each teaspoonful contains sodium 3 mg
- store between20-25°C (68-77°F)
- do not refrigerate
- dosing cup provided
- Keep carton for full direction for use

Inactive ingredients

anhydrous citric acid, dextrose, D&C red #33, FD&C red #40, flavors, glycerin, maltitol, propylene glycol, purified water, saccharin sodium, sodium benzoate, sucralose, xanthan gum

Questions?

Call weekdays from 9:30 AM to 4:30 PM EST 1-877-798-5944

Children's Cough Mucus Relief product label

DISCOUNT
drug
mart
FOOD FAIR

DO NOT USE IF PRINTED SEAL, UNDER CAP IS TORN OR MISSING

COMPARE TO THE ACTIVE INGREDIENTS IN CHILDREN'S MUCINEX® COUGH*

Children's Cough Mucus Relief

Cough Suppressent

Expectorant

Dextromethorphan HBr 5 mg

Guaifensin 100 mg

Relieves Chest Congestion

Thins & Loosens Mucus

Alcohol free
for ages 4 to 12

CHERRY FLAVOR

4 FL OX (118 ml)

* this product is not manufactured or distributed by Reckitt Benckiser Inc., the distributer of Childrens Mucinex® Cough.

SATISFACTION GUARANTEED

IF DISSATISFIED, RETURN THE UNUSED PORTION AND PACKAGE TO STORE WHERE PURCHASED. IF UNABLE TO RETURN TO STOORE, SEND REASON FOR DISSATISFACTION, NAME, ADDRESS, AND EMPTY PACKAGE TO: DISCOUNT DRUG MART, 211 COMMERCE DRIVE, MEDINA, OHIO 44256

BX-052

res